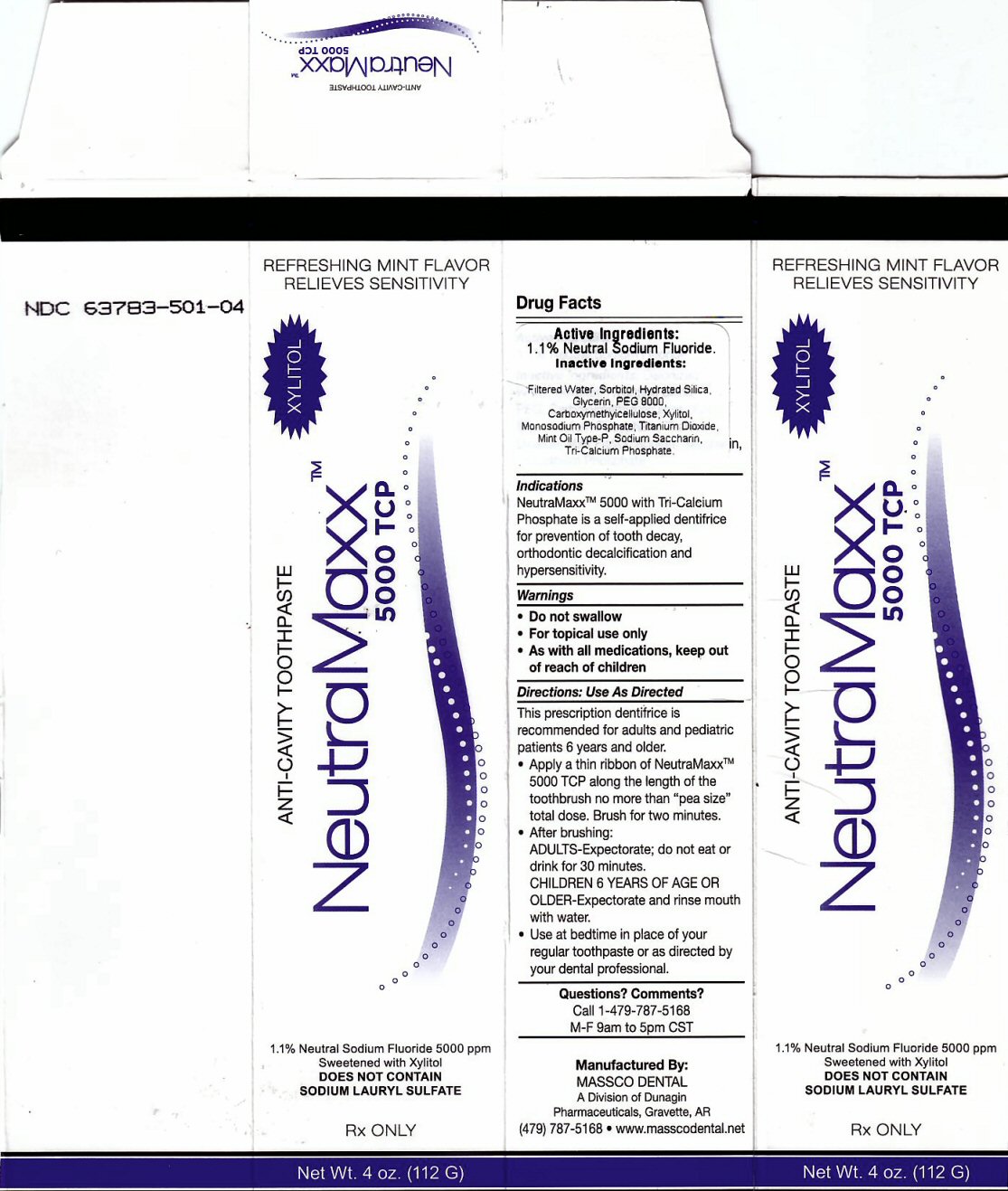 DRUG LABEL: NEUTRAMAXX 5000  TCP
NDC: 63783-501 | Form: PASTE, DENTIFRICE
Manufacturer: Massco Dental A Division of Dunagin Pharmaceuticals
Category: prescription | Type: HUMAN PRESCRIPTION DRUG LABEL
Date: 20231217

ACTIVE INGREDIENTS: SODIUM FLUORIDE 1.1 g/112 g
INACTIVE INGREDIENTS: WATER; SORBITOL; HYDRATED SILICA; POLYETHYLENE GLYCOL 8000; CARBOXYMETHYLCELLULOSE; XYLITOL; SODIUM PHOSPHATE, MONOBASIC, MONOHYDRATE ; TITANIUM DIOXIDE; SACCHARIN SODIUM; TRIBASIC CALCIUM PHOSPHATE

Active Ingredient Section

DRUG FACTS ACTIVE INGREDIENT 1.1 % NEUTRAL SODIUM FLUORIDE

Purpose Section

For prevention of tooth decay, orthodontic decalcification and hypersensitivity.

Keep Out of Reach of Children Section

As with all medications, keep out of reach of children.

Indications and Usage Section

NeutraMaxxtm 5000 with Tri-Calcium Phosphate is a self applied dentifrice for prevention of tooth decay, orthodontic decalcification and hypersensitivity

Warning Section

Warnings Do not swallow For topical use only

Directions: Use As Directed Section

This prescription dentifrice is recommended for adults and pediatric patients 6 years and older

Apply a thin ribbon of NeutraMaxxtm 5000 TCP along the length of the toothbrush no more than "pea size" total dose. Brush for two minutes.

After brushing ADULTS - Expectorate, do not eat for 30 minutes. CHILDREN 6 YEARS OF AGE OR OLDER - Expectorate and rinse mouth with water. Use at bedtime in place of your regular toothpaste or as directed by your dental professional.

Inactive Ingredient Section

Inactive Ingredients: Deionized Water, Sorbitol, Hydrated Silica, PEG, Carboxymethylcellulose, Xylitol, MonoSodium Phosphate, Titanium Dioxide, Mint Flavor, Sodium Saccharin, Tri-Calcium Phosphate

Questions? Comments? Section

Call 1-479-787-5168 M-F 9am to 5 pm CST

Package Label

REFRESHING MINT FLAVOR RELIEVES SENSITIVITY

ANTI-CAVITY TOOTHPASTE NeutraMaxx tm 5000 TCP XYLITO1.1% Neutral Sodium Fluoride 5000 ppm Sweetened with Xylitol

DOES NOT CONTAIN SODIUM LAURYL SULFATE RX ONLY Net wt. 4 oz (112 G)

Manufactured By: MASSCO DENTAL A Division of Dunagin Pharmaceuticals, Gravette, AR (479) 787-5168 www.masscodental.net

res